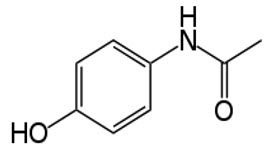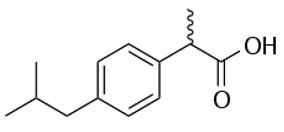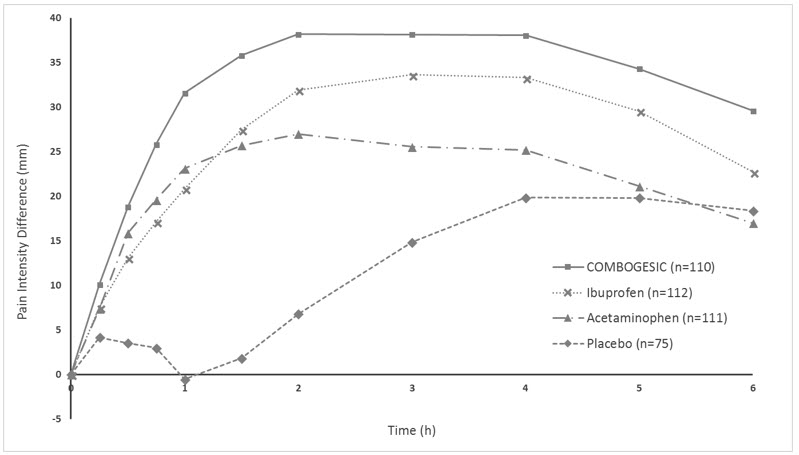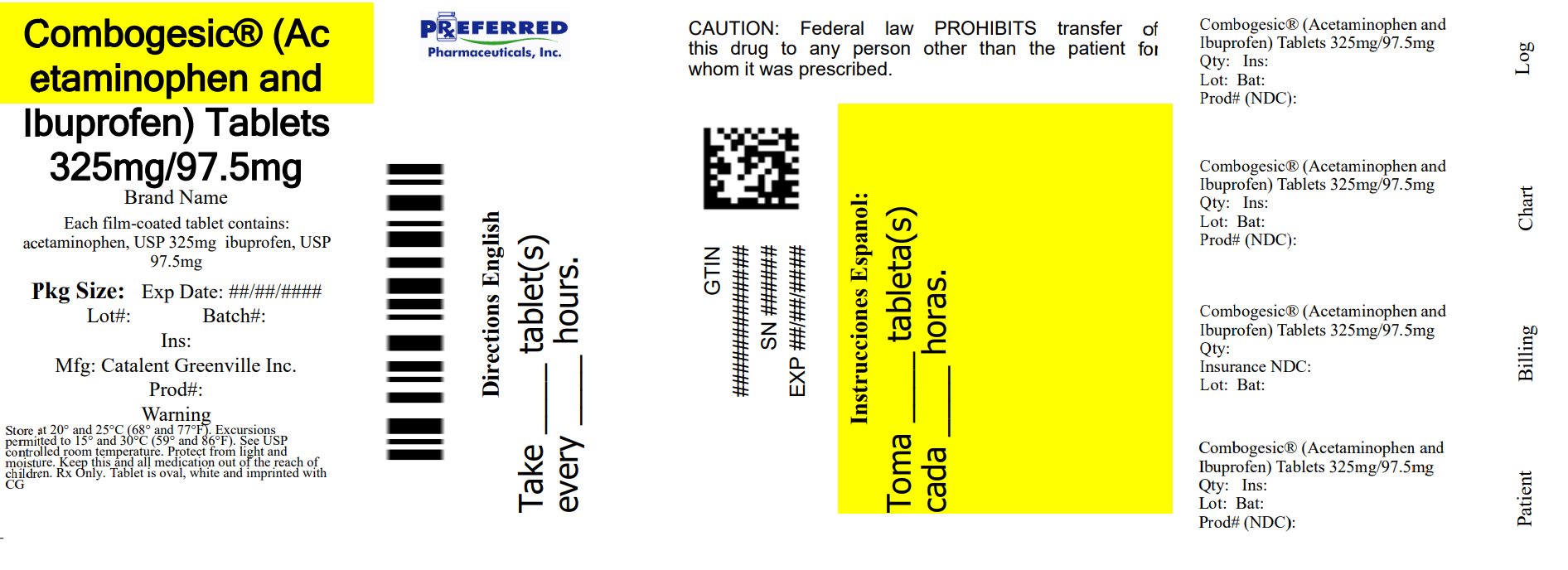 DRUG LABEL: Combogesic
NDC: 68788-4009 | Form: TABLET, FILM COATED
Manufacturer: Preferred Pharmaceuticals Inc.
Category: prescription | Type: HUMAN PRESCRIPTION DRUG LABEL
Date: 20250904

ACTIVE INGREDIENTS: ACETAMINOPHEN 325 mg/1 1; IBUPROFEN 97.5 mg/1 1
INACTIVE INGREDIENTS: SODIUM LAURYL SULFATE; MICROCRYSTALLINE CELLULOSE; POVIDONE K30; CROSCARMELLOSE SODIUM; LACTOSE MONOHYDRATE; MAGNESIUM STEARATE; HYPROMELLOSE 2910 (15 MPA.S); TITANIUM DIOXIDE; POLYDEXTROSE; TALC; MALTODEXTRIN; MEDIUM-CHAIN TRIGLYCERIDES

HIGHLIGHTS OF PRESCRIBING INFORMATION

These highlights do not include all the information needed to use COMBOGESIC safely and effectively. See full prescribing information for COMBOGESIC.
COMBOGESIC® (acetaminophen and ibuprofen) tablets, for oral use.
Initial U.S. Approval: 2023

RECENT MAJOR CHANGES

Warnings and Precautions (5.9) | 11/2024

WARNING: HEPATOTOXICITY, CARDIOVASCULAR RISK, AND GASTROINTESTINAL RISK

See full prescribing information for complete boxed warning.

- COMBOGESIC contains acetaminophen, which has been associated with cases of acute liver failure, at times resulting in liver transplant and death. Most of the cases of liver injury are associated with doses of acetaminophen that exceed 4,000 milligrams per day, and often involve more than one acetaminophen containing product (5.1).
- Nonsteroidal anti-inflammatory drugs (NSAIDS), like the ibuprofen in COMBOGESIC, cause an increased risk of serious cardiovascular thrombotic events, including myocardial infarction and stroke, which can be fatal. This risk may occur early in treatment and may increase with duration of use (5.2).
- COMBOGESIC tablets are contraindicated in the setting of coronary artery bypass graft (CABG) surgery (5.2).
- NSAIDS, like the ibuprofen in COMBOGESIC, cause an increased risk of serious gastrointestinal adverse events including bleeding, ulceration, and perforation of the stomach or intestines, which can be fatal. These events can occur at any time during use and without warning symptoms. Elderly patients and patients with a prior history of peptic ulcer disease and/or GI bleeding are at greater risk for serious GI events (5.3).

1 INDICATIONS AND USAGE

COMBOGESIC is a combination of acetaminophen and ibuprofen, a non-steroidal anti-inflammatory drug (NSAID), and is indicated in adults for the short term management of mild to moderate acute pain (1).

2 DOSAGE AND ADMINISTRATION

- Use the lowest effective dosage for shortest duration consistent with individual patient treatment goals (2).
- Do not administer with other acetaminophen-containing products (2).

Three tablets every 6 hours as needed for pain relief, up to a maximum of 12 tablets per day (2).

3 DOSAGE FORMS AND STRENGTHS

- Film-coated tablet containing 325 mg acetaminophen and 97.5 mg ibuprofen (3).

4 CONTRAINDICATIONS

COMBOGESIC is contraindicated in:

- patients with known hypersensitivity to acetaminophen, ibuprofen, other NSAIDs, or to any of the excipients in this product (4).
- patients with a history of asthma, urticaria, or other allergic-type reactions after taking aspirin or other NSAIDs. Severe, sometimes fatal, anaphylactic reactions to NSAIDs have been reported in such patients (4).
- the setting of coronary artery bypass graft (CABG) surgery (4).

5 WARNINGS AND PRECAUTIONS

- Hypertension: Patients taking some antihypertensive medications may have impaired response to these therapies when taking NSAIDs. Monitor blood pressure (5.4).
- Heart Failure and Edema: Avoid use of COMBOGESIC in patients with severe heart failure unless benefits are expected to outweigh risk of worsening heart failure (5.5).
- Renal Toxicity: Long-term administration of NSAIDs, including the ibuprofen component of COMBOGESIC, has resulted in renal papillary necrosis and other renal injury (5.6).
- Anaphylactic Reactions: Seek emergency help if an anaphylactic reaction occurs (5.7).
- Exacerbation of Asthma Related to Aspirin Sensitivity: COMBOGESIC is contraindicated in patients with aspirin-sensitive asthma. Monitor patients with preexisting asthma (without aspirin sensitivity) (5.8).
- Serious Skin Reactions: Discontinue COMBOGESIC at first appearance of skin rash or other signs of hypersensitivity (5.9).
- Drug Reaction with Eosinophilia and Systemic Symptoms (DRESS): Discontinue and evaluate clinically (5.10).
- Fetal Toxicity: Limit use of NSAID-containing products, including COMBOGESIC, between about 20 to 30 weeks in pregnancy due to the risk of oligohydramnios/fetal renal dysfunction. Avoid use of NSAID-containing products, including COMBOGESIC in women at about 30 weeks gestation and later in pregnancy due to the risks of oligohydramnios/fetal renal dysfunction and premature closure of the fetal ductus arteriosus (5.11).
- Hematologic Toxicity: Monitor hemoglobin or hematocrit in patients with any signs or symptoms of anemia (5.12).

6 ADVERSE REACTIONS

The most common adverse reactions (greater than or equal to 2%) are nausea, vomiting, headache, dizziness, somnolence, post-procedural hemorrhage, and swelling of the face (6).

To report SUSPECTED ADVERSE REACTIONS, contact AFT Pharmaceuticals US, Inc at 01-248-631-4810 or FDA at 1-800-FDA-1088 or www.fda.gov/medwatch.

7 DRUG INTERACTIONS

A number of known or potential interactions between COMBOGESIC and other drugs/drug classes exist. Please refer to the Drug Interactions section (7) for further information.

8 USE IN SPECIFIC POPULATIONS

- Infertility: NSAID-containing products, including COMBOGESIC, are associated with reversible infertility. Consider withdrawal of COMBOGESIC tablets in women who have difficulties conceiving. (8.3)
- Renal or hepatic impairment: Not recommended (5.1, 5.6, 8.6, 8.7).

FULL PRESCRIBING INFORMATION

WARNING: HEPATOTOXICITY, CARDIOVASCULAR RISK, AND GASTROINTESTINAL RISK

HEPATOTOXICITY

COMBOGESIC contains acetaminophen. Acetaminophen has been associated with cases of acute liver failure, at times resulting in liver transplant and death. Most of the cases of liver injury are associated with the use of acetaminophen at doses that exceed 4,000 milligrams per day, and often involve more than one acetaminophen-containing product [see Warnings and Precautions (5.1)].

CARDIOVASCULAR RISK

COMBOGESIC contains ibuprofen, a nonsteroidal anti-inflammatory drug (NSAID). NSAIDs cause an increased risk of serious cardiovascular thrombotic events, including myocardial infarction, and stroke, which can be fatal. This risk may occur early in treatment and may increase with duration of use [see Warnings and Precautions (5.2)].

COMBOGESIC is contraindicated for treatment of peri-operative pain in the setting of coronary artery bypass graft (CABG) surgery [see Warnings and Precautions (5.2)].

GASTROINTESTINAL RISK

NSAIDS cause an increased risk of serious gastrointestinal adverse events including bleeding, ulceration, and perforation of the stomach or intestines, which can be fatal. These events can occur at any time during use and without warning symptoms. Elderly patients and patients with a prior history of peptic ulcer disease and/or GI bleeding are at greater risk for serious GI events [see Warnings and Precautions (5.3)].

1 INDICATIONS AND USAGE

COMBOGESIC is indicated in adults for the short-term management of mild to moderate acute pain.

2 DOSAGE AND ADMINISTRATION

- Use the lowest effective dosage for the shortest duration consistent with individual patient treatment goals [see Warnings and Precautions (5)].
- Do not exceed the recommended dose of COMBOGESIC in 24 hours [see (2) below].
- Do not co-administer COMBOGESIC with other acetaminophen- or NSAID-containing products [see Warnings and Precautions (5.1, 5.2, 5.3)].

The recommended dose of COMBOGESIC is 3 tablets every 6 hours as needed for pain relief, up to a maximum of 12 tablets per day.

3 DOSAGE FORMS AND STRENGTHS

Tablets: white, biconvex, capsule-shaped, film-coated tablets, debossed with the letters "CG" on one side and plain on the other side, each containing 325 mg acetaminophen and 97.5 mg ibuprofen.

4 CONTRAINDICATIONS

COMBOGESIC is contraindicated in:

- patients with a known hypersensitivity (e.g., anaphylactic reactions, serious skin reactions) to acetaminophen, ibuprofen, other NSAIDs, or to any of the excipients in this product [see Warnings and Precautions (5.7, 5.8, 5.9)].
- patients with a history of asthma, urticaria, or other allergic-type reactions after taking aspirin or other NSAIDS [see Warnings and Precautions (5.7 and 5.8)].
- the setting of coronary artery bypass graft (CABG) surgery [see Warnings and Precautions (5.2)].

5 WARNINGS AND PRECAUTIONS

5.1 Hepatotoxicity

Acetaminophen

COMBOGESIC contains acetaminophen. Acetaminophen has been associated with cases of acute liver failure, at times resulting in liver transplant and death. Most of the cases of liver injury are associated with the use of acetaminophen at doses that exceed 4,000 milligrams per day, and often involved more than one acetaminophen-containing product. The excessive intake of acetaminophen may be intentional to cause self-harm or unintentional as patients attempt to obtain more pain relief or unknowingly take other acetaminophen-containing products.

The risk of acute liver failure is higher in individuals with underlying liver disease and in individuals who ingest alcohol while taking acetaminophen.

Instruct patients to look for acetaminophen or APAP on package labels and not to use more than one product that contains acetaminophen. Instruct patients to seek medical attention immediately upon ingestion of more than 4,000 milligrams of acetaminophen per day, even if they feel well.

Ibuprofen

Elevations of ALT or AST (three or more times the upper limit of normal [ULN]) have been reported in approximately 1% of NSAID-treated patients in clinical trials. In addition, rare, sometimes fatal, cases of severe hepatic injury, including fulminant hepatitis, liver necrosis, and hepatic failure have been reported.

Elevations of ALT or AST (less than three times ULN) may occur in up to 15% of patients treated with NSAIDs including ibuprofen.

Inform patients of the warning signs and symptoms of hepatotoxicity (e.g., nausea, fatigue, lethargy, diarrhea, pruritus, jaundice, right upper quadrant tenderness, and "flu-like" symptoms). If clinical signs and symptoms consistent with liver disease develop, or if systemic manifestations occur (e.g., eosinophilia, rash, etc.), discontinue COMBOGESIC immediately, and perform a clinical evaluation of the patient.

COMBOGESIC has not been studied in patients with impaired hepatic function. The use of COMBOGESIC in patients with hepatic impairment is not recommended.

5.2 Cardiovascular Thrombotic Events

Clinical trials of several COX-2 selective and nonselective NSAIDs of up to three years duration have shown an increased risk of serious cardiovascular (CV) thrombotic events, including myocardial infarction (MI), and stroke, which can be fatal. Based on available data, it is unclear that the risk for CV thrombotic events is similar for all NSAIDs. The relative increase in serious CV thrombotic events over baseline conferred by NSAID use appears to be similar in those with and without known CV disease or risk factors for CV disease. However, patients with known CV disease or risk factors had a higher absolute incidence of excess serious CV thrombotic events, due to their increased baseline rate. Some observational studies found that this increased risk of serious CV thrombotic events began as early as the first weeks of treatment. The increase in CV thrombotic risk has been observed most consistently at higher doses.

To minimize the potential risk for an adverse CV event in NSAID-treated patients, use the lowest effective dose for the shortest duration possible. Physicians and patients should remain alert for the development of such events, throughout the entire treatment course, even in the absence of previous CV symptoms. Patients should be informed about the signs and/or symptoms of serious CV events and the steps to take if they occur.

There is no consistent evidence that concurrent use of aspirin mitigates the increased risk of serious CV thrombotic events associated with NSAID use. The concurrent use of aspirin and an NSAID, such as ibuprofen, increases the risk of serious gastrointestinal (GI) events [see Warnings and Precautions (5.3)].

Status Post Coronary Artery Bypass Graft (CABG) Surgery

Two large, controlled clinical trials of a COX-2 selective NSAID for the treatment of pain in the first 10-14 days following CABG surgery found an increased incidence of myocardial infarction and stroke. NSAIDs are contraindicated in the setting of CABG [see Contraindications (4)].

Post-MI Patients

Observational studies conducted in the Danish National Registry have demonstrated that patients treated with NSAIDs in the post-MI period were at increased risk of reinfarction, CV-related death, and all-cause mortality beginning in the first week of treatment. In this same cohort, the incidence of death in the first year post-MI was 20 per 100 person years in NSAID-treated patients compared to 12 per 100 person years in non-NSAID exposed patients. Although the absolute rate of death declined somewhat after the first year post-MI, the increased relative risk of death in NSAID users persisted over at least the next four years of follow-up.

Avoid the use of COMBOGESIC in patients with a recent MI unless the benefits are expected to outweigh the risk of recurrent CV thrombotic events. If COMBOGESIC is used in patients with a recent MI, monitor patients for signs of cardiac ischemia.

5.3 Gastrointestinal Bleeding, Ulceration, and Perforation

NSAIDs, including the ibuprofen in COMBOGESIC tablets, can cause serious gastrointestinal (GI) adverse events including inflammation, bleeding, ulceration, and perforation of the esophagus, stomach, small intestine, or large intestine, which can be fatal. These serious adverse events can occur at any time, with or without warning symptoms, in patients treated with NSAIDs. Only one in five patients, who develop a serious upper GI adverse event on NSAID therapy, is symptomatic. Upper GI ulcers, gross bleeding, or perforation caused by NSAIDs occur in approximately 1% of patients treated for 3-6 months, and in about 2-4% of patients treated for one year. However, even short-term therapy is not without risk.

Risk Factors for Bleeding, Ulceration, and Perforation

Patients with a prior history of peptic ulcer disease and/or gastrointestinal bleeding who used NSAIDs had a greater than 10-fold increased risk for developing a GI bleed compared to patients without these risk factors. Other factors that increase the risk of GI bleeding in patients treated with NSAIDs include longer duration of NSAID therapy, concomitant use of oral corticosteroids, aspirin, anticoagulants, or selective serotonin reuptake inhibitors (SSRIs); smoking; use of alcohol; older age; and poor general health status. Most postmarketing reports of fatal GI events occurred in elderly or debilitated patients. Additionally, patients with advanced liver disease and/or coagulopathy are at increased risk for GI bleeding.

Strategies to Minimize the GI Risks in NSAID-treated patients:

- Use the lowest effective dosage for the shortest possible duration.
- Avoid administration of more than one NSAID at a time.
- Avoid use in patients at higher risk unless the benefits are expected to outweigh the increased risk of bleeding. For such patients, as well as those with active GI bleeding, consider alternative therapies other than NSAIDs.
- Remain alert for signs and symptoms of GI ulcerations and bleeding during NSAID therapy.
- If a serious GI adverse event is suspected, promptly initiate additional evaluation and treatment, and discontinue COMBOGESIC until a serious GI adverse event is ruled out.
- In the setting of concomitant use of low-dose aspirin for cardiac prophylaxis, monitor patients more closely for evidence of GI bleeding [see Drug Interactions (7)].

5.4 Hypertension

NSAIDs, including the ibuprofen in COMBOGESIC, can lead to onset of new hypertension or worsening of preexisting hypertension, either of which may contribute to the increased incidence of CV events. Patients taking angiotensin converting enzyme (ACE) inhibitors, thiazide diuretics, or loop diuretics may have impaired response to these therapies when taking NSAIDs. Monitor blood pressure (BP) during the initiation of NSAID treatment and throughout the course of therapy.

5.5 Heart Failure and Edema

The Coxib and traditional NSAID Trialists' Collaboration meta-analysis of randomized controlled trials demonstrated an approximately two-fold increase in hospitalizations for heart failure in COX-2 selective-treated patients and nonselective NSAID-treated patients compared to placebo-treated patients. In a Danish National Registry study of patients with heart failure, NSAID use increased the risk of MI, hospitalization for heart failure, and death.

Additionally, fluid retention and edema have been observed in some patients treated with NSAIDs. Use of ibuprofen may blunt the CV effects of several therapeutic agents used to treat these medical conditions (e.g., diuretics, ACE inhibitors, or angiotensin receptor blockers [ARBs]) [see Drug Interactions (7)].

Avoid the use of COMBOGESIC in patients with severe heart failure unless the benefits are expected to outweigh the risk of worsening heart failure. If COMBOGESIC is used in patients with severe heart failure, monitor patients for signs of worsening heart failure.

5.6 Renal Toxicity and Hyperkalemia

Renal Toxicity

Long-term administration of NSAIDs, including the ibuprofen component of COMBOGESIC, has resulted in renal papillary necrosis and other renal injury.

Renal toxicity has also been seen in patients in whom renal prostaglandins have a compensatory role in the maintenance of renal perfusion. In these patients, administration of a NSAID may cause a dose-dependent reduction in prostaglandin formation and, secondarily, in renal blood flow, which may precipitate overt renal decompensation. Patients at greatest risk of this reaction are those with impaired renal function, dehydration, hypovolemia, heart failure, liver dysfunction, those taking diuretics and ACE inhibitors or ARBs, and the elderly. Discontinuation of NSAID therapy is usually followed by recovery to the pretreatment state.

Hyperkalemia

Increases in serum potassium concentration, including hyperkalemia, have been reported with use of NSAIDs, even in some patients without renal impairment. In patients with normal renal function, these effects have been attributed to a hyporeninemic-hypoaldosteronism state.

5.7 Anaphylaxis and Other Hypersensitivity Reactions

Acetaminophen

There have been postmarketing reports of hypersensitivity and anaphylaxis associated with the use of acetaminophen. Clinical signs included swelling of the face, mouth, and throat, respiratory distress, urticaria, rash, pruritus, and vomiting. There were infrequent reports of life-threatening anaphylaxis requiring emergency medical attention. Instruct patients to discontinue COMBOGESIC immediately and seek emergency medical care if they experience these symptoms. Do not prescribe COMBOGESIC for patients with acetaminophen allergy [see Contraindications (4)].

Ibuprofen

NSAIDs, including the ibuprofen in COMBOGESIC, has been associated with anaphylactic reactions in patients with and without known hypersensitivity to ibuprofen and in patients with aspirin-sensitive asthma. Instruct patients to discontinue COMBOGESIC immediately and seek emergency medical care if they experience these symptoms. Do not prescribe COMBOGESIC for patients with ibuprofen or NSAID allergy [see Contraindications (4) and Warnings and Precautions (5.8)].

5.8 Exacerbation of Asthma Related to Aspirin Sensitivity

A subpopulation of patients with asthma may have aspirin-sensitive asthma which may include chronic rhinosinusitis complicated by nasal polyps; severe, potentially fatal bronchospasm; and/or intolerance to aspirin and other NSAIDs. Because cross-reactivity between aspirin and other NSAIDs has been reported in such aspirin-sensitive patients, COMBOGESIC is contraindicated in patients with this form of aspirin sensitivity [see Contraindications (4)]. When COMBOGESIC is used in patients with preexisting asthma (without known aspirin sensitivity), monitor patients for changes in the signs and symptoms of asthma.

5.9 Serious Skin Reactions

COMBOGESIC contains acetaminophen and ibuprofen. Acetaminophen or NSAIDs, including ibuprofen, may cause serious skin adverse events such as exfoliative dermatitis, acute generalized exanthematous pustulosis (AGEP), Stevens-Johnson Syndrome (SJS), and toxic epidermal necrolysis (TEN), which can be fatal. NSAIDs can also cause fixed drug eruption (FDE). FDE may present as a more severe variant known as generalized bullous fixed drug eruption (GBFDE), which can be life-threatening. These serious events may occur without warning. Inform patients about the signs and symptoms of serious skin reactions and to discontinue the use of COMBOGESIC at the first appearance of skin rash or any other sign of hypersensitivity. COMBOGESIC is contraindicated in patients with previous serious skin reactions to acetaminophen or NSAIDs [see Contraindications (4)].

5.10 Drug Reaction with Eosinophilia and Systemic Symptoms (DRESS)

Drug Reaction with Eosinophilia and Systemic Symptoms (DRESS) has been reported in patients taking NSAIDs, such as the ibuprofen in COMBOGESIC. Some of these events have been fatal or life-threatening. DRESS typically, although not exclusively, presents with fever, rash, lymphadenopathy, and/or facial swelling. Other clinical manifestations may include hepatitis, nephritis, hematological abnormalities, myocarditis, or myositis. Sometimes symptoms of DRESS may resemble an acute viral infection. Eosinophilia is often present. Because this disorder is variable in its presentation, other organ systems not noted here may be involved. It is important to note that early manifestations of hypersensitivity, such as fever or lymphadenopathy, may be present even though rash is not evident. If such signs or symptoms are present, discontinue COMBOGESIC and evaluate the patient immediately.

5.11 Fetal Toxicity

Premature Closure of Fetal Ductus Arteriosus

Avoid use of NSAID-containing products, including COMBOGESIC, in pregnant women at about 30 weeks gestation and later. NSAID-containing products, including COMBOGESIC, increase the risk of premature closure of the fetal ductus arteriosus at approximately this gestational age.

Oligohydramnios/Neonatal Renal Impairment:

Use of NSAID-containing products, including COMBOGESIC, at about 20 weeks gestation or later in pregnancy may cause fetal renal dysfunction leading to oligohydramnios and, in some cases, neonatal renal impairment. These adverse outcomes are seen, on average, after days to weeks of treatment, although oligohydramnios has been infrequently reported as soon as 48 hours after NSAID initiation. Oligohydramnios is often, but not always, reversible with treatment discontinuation. Complications of prolonged oligohydramnios may, for example, include limb contractures and delayed lung maturation. In some post-marketing cases of impaired neonatal renal function, invasive procedures such as exchange transfusion or dialysis were required.

If, after careful consideration of alternative treatment options for pain management, NSAID- treatment is necessary between about 20 weeks and 30 weeks gestation, limit COMBOGESIC use to the lowest effective dose and shortest duration possible. Consider ultrasound monitoring of amniotic fluid if COMBOGESIC treatment extends beyond 48 hours. Discontinue COMBOGESIC if oligohydramnios occurs and follow up according to clinical practice [see Use in Specific Populations (8.1)].

5.12 Hematologic Toxicity

Anemia has occurred in NSAID-treated patients. This may be due to occult or gross GI blood loss, fluid retention, or an incompletely described effect upon erythropoiesis. If a patient treated with COMBOGESIC has any signs or symptoms of anemia, monitor hemoglobin or hematocrit.

NSAIDs, including the ibuprofen in COMBOGESIC, may increase the risk of bleeding events. Co-morbid conditions such as coagulation disorders or concomitant use of warfarin, other anticoagulants, antiplatelet agents (e.g., aspirin), serotonin reuptake inhibitors (SSRIs) and serotonin norepinephrine reuptake inhibitors (SNRIs) may increase this risk. Monitor these patients for signs of bleeding [see Drug Interactions (7)].

5.13 Ophthalmological Effects

Blurred and/or diminished vision, scotomata, and/or changes in color vision have been reported in patients receiving ibuprofen. If a patient develops such complaints while receiving COMBOGESIC, the drug should be discontinued, and the patient should have an ophthalmologic examination which includes central visual fields and color vision testing.

5.14 Aseptic Meningitis

Aseptic meningitis with fever and coma has been observed on rare occasions in patients on ibuprofen therapy. Although it is probably more likely to occur in patients with systemic lupus erythematosus and related connective tissue diseases, it has been reported in patients who do not have an underlying chronic disease. If signs or symptoms of meningitis develop in a patient on COMBOGESIC, the possibility of its being related to ibuprofen should be considered.

5.15 Masking of Inflammation and Fever

The pharmacological activity of COMBOGESIC in reducing inflammation, and possibly fever, may diminish the utility of diagnostic signs in detecting infections.

5.16 Laboratory Monitoring

Because serious GI bleeding, hepatotoxicity, and renal injury can occur without warning symptoms or signs, consider monitoring patients on long-term NSAID treatment with a CBC and a chemistry profile periodically [see Warnings and Precautions (5.1, 5.3, 5.6)].

6 ADVERSE REACTIONS

The following clinically significant adverse reactions to ibuprofen or acetaminophen are described elsewhere in other sections of the labelling.

- Hepatotoxicity [see Warnings and Precautions (5.1)]
- Cardiovascular Thrombotic Events [see Warnings and Precautions (5.2)]
- Gastrointestinal Bleeding, Ulceration, and Perforation [see Warnings and Precautions (5.3)]
- Hypertension [see Warnings and Precautions (5.4)]
- Heart Failure and Edema [see Warnings and Precautions (5.5)]
- Renal Toxicity and Hyperkalemia [see Warnings and Precautions (5.6)]
- Anaphylaxis and Other Hypersensitivity Reactions [see Warnings and Precautions (5.7)]
- Serious Skin Reactions [see Warnings and Precautions (5.9)]
- Hematologic Toxicity [see Warnings and Precautions (5.12)]

The most common adverse reactions (incidence of ≥ 2% for patients receiving COMBOGESIC) are: nausea, vomiting, headache, dizziness, somnolence, post-procedural hemorrhage, and swelling of the face (Table 1).

6.1 Clinical Trials Experience

Because clinical trials are conducted under varying conditions, adverse reaction rates observed in the clinical trials of one drug cannot be directly compared to the rates reported from clinical trials of another drug and may not reflect the rates observed in practice.

The clinical trials of COMBOGESIC have been conducted in patients with postoperative pain following dental and arthroscopic procedures, who received double-blind treatment every 6 hours for 24 or 48 hours.

Most commonly (≥2%) reported adverse reactions by organ system during double-blind treatment are listed in the table below. Adverse reactions are closely related to the extent (the level and length) of exposure. The incidences of overall and individual adverse reactions reported during the double-blind treatment period did not suggest an increase of risks associated with short-term (up to one or two days) use of the combination drug, COMBOGESIC in comparison to each individual component, acetaminophen or ibuprofen, and to placebo.

Table 1: Most commonly (≥2%) reported adverse reactions by organ system during double-blind treatment
 | COMBOGESIC | Acetaminophen | Ibuprofen | Placebo
 | N=261 | N=231 | N=231 | N=199
Total number of AEs | 145 | 142 | 101 | 133
% of patients with ≥1 AE | 30 | 38 | 29 | 37
Gastrointestinal disorders
Nausea | 15 | 19 | 12 | 23
Vomiting | 7 | 10 | 3 | 10
Constipation | 1 | 2 | 1 | 1
Dyspepsia | 0.4 | 1 | 2 | 1
Injury, poisoning and procedural complications
Post Procedural Hemorrhage | 2 | 0.4 | 1 | 2
Nervous system disorders
Headache | 5 | 6 | 4 | 7
Dizziness | 3 | 4 | 4 | 5
Somnolence | 2 | 1 | 0 | 1
Skin and subcutaneous tissue disorders
Swelling face | 2 | 4 | 4 | 3
Pruritus | 0.4 | 0.4 | 0.4 | 3

6.2 Postmarketing Experience

The following adverse reactions have been identified during postapproval use of acetaminophen and ibuprofen. Because these reactions are reported voluntarily from a population of uncertain size, it is not always possible to reliably estimate their frequency or establish a causal relationship to drug exposure.

Skin and Appendages: Exfoliative dermatitis, Stevens-Johnson Syndrome (SJS), toxic epidermal necrolysis (TEN), and fixed drug eruption (FDE).

7 DRUG INTERACTIONS

Table 2: Clinically Significant Drug Interactions with COMBOGESIC
Drugs That Interfere with Hemostasis
Clinical Impact: | - Ibuprofen and anticoagulants such as warfarin have a synergistic effect on bleeding. The concomitant use of ibuprofen and anticoagulants have an increased risk of serious bleeding compared to the use of either drug alone. - Serotonin release by platelets plays an important role in hemostasis. Case-control and cohort epidemiological studies showed that concomitant use of drugs that interfere with serotonin reuptake and an NSAID may potentiate the risk of bleeding more than an NSAID alone.
Intervention: | Monitor patients with concomitant use of COMBOGESIC with anticoagulants (e.g., warfarin), antiplatelet agents (e.g., aspirin), selective serotonin reuptake inhibitors (SSRIs), and serotonin norepinephrine reuptake inhibitors (SNRIs) for signs of bleeding [see Warnings and Precautions (5.12)].
Aspirin
Clinical Impact: | Controlled clinical studies showed that the concomitant use of NSAIDs and analgesic doses of aspirin does not produce any greater therapeutic effect than the use of NSAIDs alone. In a clinical study, the concomitant use of an NSAID and aspirin was associated with a significantly increased incidence of GI adverse reactions as compared to use of the NSAID alone [see Warnings and Precautions (5.3)].
Intervention: | Concomitant use of COMBOGESIC and analgesic doses of aspirin is not generally recommended because of the increased risk of bleeding [see Warnings and Precautions (5.3)]. COMBOGESIC is not a substitute for low dose aspirin for cardiovascular protection.
ACE Inhibitors, Angiotensin Receptor Blockers, and Beta-Blockers
Clinical Impact: | - NSAIDs may diminish the antihypertensive effect of angiotensin converting enzyme (ACE) inhibitors, angiotensin receptor blockers (ARBs), or beta-blockers (including propranolol). - In patients who are elderly, volume-depleted (including those on diuretic therapy), or have renal impairment, co-administration of an NSAID with ACE inhibitors or ARBs may result in deterioration of renal function, including possible acute renal failure. These effects are usually reversible.
Intervention: | - During concomitant use of COMBOGESIC and ACE-inhibitors, ARBs, or beta-blockers, monitor blood pressure to ensure that the desired blood pressure is obtained. - During concomitant use of COMBOGESIC and ACE-inhibitors or ARBs in patients who are elderly, volume-depleted, or have impaired renal function, monitor for signs of worsening renal function [see Warnings and Precautions (5.6)]. - When these drugs are administered concomitantly, patients should be adequately hydrated. Assess renal function at the beginning of the concomitant treatment and periodically thereafter.
Diuretics
Clinical Impact: | Clinical studies, as well as post-marketing observations, showed that NSAIDs reduced the natriuretic effect of loop diuretics (e.g., furosemide) and thiazide diuretics in some patients. This effect has been attributed to the NSAID inhibition of renal prostaglandin synthesis.
Intervention: | During concomitant use of COMBOGESIC with diuretics, observe patients for signs of worsening renal function, in addition to assuring diuretic efficacy including antihypertensive effects [see Warnings and Precautions (5.4 and 5.6)].
Digoxin
Clinical Impact: | The concomitant use of ibuprofen with digoxin has been reported to increase the serum concentration and prolong the half-life of digoxin.
Intervention: | During concomitant use of COMBOGESIC and digoxin, monitor serum digoxin levels.
Lithium
Clinical Impact: | NSAIDs have produced elevations in plasma lithium levels and reductions in renal lithium clearance. The mean minimum lithium concentration increased 15%, and the renal clearance decreased by approximately 20%. This effect has been attributed to NSAID inhibition of renal prostaglandin synthesis.
Intervention: | During concomitant use of COMBOGESIC and lithium, monitor patients for signs of lithium toxicity.
Methotrexate
Clinical Impact: | Concomitant use of NSAIDs and methotrexate may increase the risk for methotrexate toxicity (e.g., neutropenia, thrombocytopenia, renal dysfunction).
Intervention: | During concomitant use of COMBOGESIC and methotrexate, monitor patients for methotrexate toxicity.
Cyclosporine
Clinical Impact: | Concomitant use of NSAIDS and cyclosporine may increase cyclosporine's nephrotoxicity.
Intervention: | During concomitant use of COMBOGESIC and cyclosporine, monitor patients for signs of worsening renal function.
NSAIDs and Salicylates
Clinical Impact: | Concomitant use of ibuprofen with other NSAIDs or salicylates (e.g., diflunisal, salsalate) increases the risk of GI toxicity, with little or no increase in efficacy [see Warnings and Precautions (5.3)].
Intervention: | The concomitant use of ibuprofen with other NSAIDs or salicylates is not recommended.
Pemetrexed
Clinical Impact: | Concomitant use of NSAIDS and pemetrexed may increase the risk of pemetrexed-associated myelosuppression, renal, and GI toxicity (see the pemetrexed prescribing information).
Intervention: | During concomitant use of COMBOGESIC and pemetrexed, in patients with renal impairment whose creatinine clearance ranges from 45 to 79 mL/min, monitor for myelosuppression, renal and GI toxicity. NSAIDs with short elimination half-lives (e.g., diclofenac, indomethacin) should be avoided for a period of two days before, the day of, and two days following administration of pemetrexed. In the absence of data regarding potential interaction between pemetrexed and NSAIDs with longer half-lives (e.g., meloxicam, nabumetone), patients taking these NSAIDs should interrupt dosing for at least five days before, the day of, and two days following pemetrexed administration.

8 USE IN SPECIFIC POPULATIONS

8.1 Pregnancy

Risk Summary

Ibuprofen

Use of NSAID-containing products, including COMBOGESIC, can cause premature closure of the fetal ductus arteriosus and fetal renal dysfunction leading to oligohydramnios and, in some cases, neonatal renal impairment. Because of these risks, limit dose and duration of COMBOGESIC use between about 20 and 30 weeks of gestation and avoid COMBOGESIC use at about 30 weeks of gestation and later in pregnancy (see Clinical Considerations, Data).

Premature Closure of Fetal Ductus Arteriosus:

Use of NSAID-containing products, including COMBOGESIC, at about 30 weeks gestation or later in pregnancy increases the risk of premature closure of the fetal ductus arteriosus.

Oligohydramnios/Neonatal Renal Impairment:

Use of NSAID-containing products, including COMBOGESIC, at about 20 weeks gestation or later in pregnancy has been associated with cases of fetal renal dysfunction leading to oligohydramnios, and in some cases, neonatal renal impairment.

Data from observational studies regarding other potential embryofetal risks of NSAID use in women in the first or second trimester of pregnancy are inconclusive.

In published animal reproduction studies, there were no clear developmental effects at doses up to 2.7-times the maximum human daily dose (MHDD) in the rabbit and 1.5-times in the MHDD rat when dosed throughout gestation. In contrast, an increase in membranous ventricular septal defects was reported in rats treated on Gestation Days 9 & 10 with 2.2-times the MHDD.

Based on animal data, prostaglandins have been shown to have an important role in endometrial vascular permeability, blastocyst implantation, and decidualization. In animal studies, administration of prostaglandin synthesis inhibitors such as ibuprofen, resulted in increased pre- and post-implantation loss. Prostaglandins also have been shown to have an important role in fetal kidney development. In published animal studies, prostaglandin synthesis inhibitors have been reported to impair kidney development when administered at clinically relevant doses.

Acetaminophen

Prolonged experience with acetaminophen in pregnant women over several decades, based on published observational epidemiological studies and case reports, did not identify a drug associated risk of major birth defects, miscarriage or other adverse maternal or fetal outcomes (see Data). Reproductive and developmental studies in rats and mice from the published literature have identified adverse events at clinically relevant doses of acetaminophen. Fetotoxicity, increases in bone variations in the fetuses, and necrosis in the fetus liver and kidney have been noted in studies in rats. In mice treated with acetaminophen at doses within the clinical dosing range, cumulative adverse effects on reproduction were seen in a continuous breeding study. A reduction in number of litters of the parental mating pair was observed as well as retarded growth and abnormal sperm in their offspring and reduced birth weight in the next generation.

The estimated background risk of major birth defects and miscarriage for the indicated population is unknown. All pregnancies have a background risk of birth defect, loss, or other adverse outcomes. In the U.S. general population, the estimated background risk of major birth defects and miscarriage in clinically recognized pregnancies is 2% to 4% and 15% to 20%, respectively.

Clinical Considerations

Fetal/Neonatal Adverse Reactions

Premature Closure of Fetal Ductus Arteriosus:

Avoid use of NSAID-containing products, including COMBOGESIC, in women at about 30 weeks gestation and later in pregnancy, because NSAID-containing products, including COMBOGESIC, can cause premature closure of the fetal ductus arteriosus (see Data).

Oligohydramnios/Neonatal Renal Impairment:

If, after consideration of alternative treatments for pain management, an NSAID-containing product, including COMBOGESIC, is necessary at about 20 weeks gestation or later in pregnancy, limit the use to the lowest effective dose and shortest duration possible. If COMBOGESIC treatment extends beyond 48 hours, consider monitoring with ultrasound for oligohydramnios. If oligohydramnios occurs, discontinue COMBOGESIC and follow up according to clinical practice (see Data).

Labor or Delivery

There are no studies on the effects of COMBOGESIC during labor or delivery. In animal studies, NSAIDs, including ibuprofen, inhibit prostaglandin synthesis, cause delayed parturition, and increase the incidence of stillbirth.

Data

Human Data

Ibuprofen:

Premature Closure of Fetal Ductus Arteriosus

Published literature reports that the use of NSAIDs at about 30 weeks of gestation and later in pregnancy may cause premature closure of the fetal ductus arteriosus.

Oligohydramnios/Neonatal Renal Impairment

Published studies and postmarketing reports describe maternal NSAID use at about 20 weeks gestation or later in pregnancy associated with fetal renal dysfunction leading to oligohydramnios, and in some cases, neonatal renal impairment. These adverse outcomes are seen, on average, after days to weeks of treatment, although oligohydramnios has been infrequently reported as soon as 48 hours after NSAID initiation. In many cases, but not all, the decrease in amniotic fluid was transient and reversible with cessation of the drug. There have been a limited number of case reports of maternal NSAID use and neonatal renal dysfunction without oligohydramnios, some of which were irreversible. Some cases of neonatal renal dysfunction required treatment with invasive procedures, such as exchange transfusion or dialysis.

Methodological limitations of these postmarketing studies and reports include lack of a control group; limited information regarding dose, duration, and timing of drug exposure; and concomitant use of other medications. These limitations preclude establishing a reliable estimate of the risk of adverse fetal and neonatal outcomes with maternal NSAID use. Because the published safety data on neonatal outcomes involved mostly preterm infants, the generalizability of certain reported risks to the full-term infant exposed to NSAIDs through maternal use is uncertain.

Acetaminophen:

The results from a large population-based prospective cohort, including data from 26,424 women with live born singletons who were exposed to oral acetaminophen during the first trimester, indicate no increased risk for congenital malformations, compared to a control group of unexposed children. The rate of congenital malformations (4.3%) was similar to the rate in the general population. A population-based, case-control study from the National Birth Defects Prevention Study showed that 11,610 children with prenatal exposure to acetaminophen during the first trimester had no increased risk of major birth defects compared to 4,500 children in the control group. Other epidemiological data showed similar results. However, these studies cannot definitely establish the absence of any risk because of methodological limitations, including recall bias.

Animal Data

Ibuprofen:

In a published study, female rabbits given 7.5, 20, or 60 mg/kg ibuprofen (0.12, 0.33, or 0.99-times the maximum human daily dose of 1170 mg of ibuprofen based on a body surface area comparison) from Gestation Days 1 to 29, no clear treatment-related adverse developmental effects were noted. This dose was associated with significant maternal toxicity (stomach ulcers, gastric lesions). In the same publication, female rats were administered 7.5, 20, 60, 180 mg/kg ibuprofen (0.06, 0.17, 0.50, 1.5-times the maximum daily dose) did not result in clear adverse developmental effects. Maternal toxicity (gastrointestinal lesions) was noted at 20 mg/kg and above.

In a published study, rats were orally dosed with 300 mg/kg ibuprofen (2.5-times the maximum human daily dose of 1170 mg based on a body surface area comparison) during Gestation Days 9 and 10 (critical time points for heart development in rats). Ibuprofen treatment resulted in an increase in the incidence of membranous ventricular septal defects. This dose was associated with significant maternal toxicity including gastrointestinal toxicity. One incidence each of a membranous ventricular septal defect and gastroschisis was noted fetuses from rabbits treated with 500 mg/kg (8.3-times the maximum human daily dose) from Gestation Day 9 to 11.

Acetaminophen:

Studies in pregnant rats that received oral acetaminophen during organogenesis at doses up to 0.87-times the maximum human daily dose (MHDD = 3.9 grams/day, based on a body surface area comparison) showed evidence of fetotoxicity (reduced fetal weight and length) and a dose-related increase in bone variations (reduced ossification and rudimentary rib changes). Offspring had no evidence of external, visceral, or skeletal malformations.

When pregnant rats received oral acetaminophen throughout gestation at doses of 1.2-times the MHDD (based on a body surface area comparison), areas of necrosis occurred in both the liver and kidney of pregnant rats and fetuses. These effects did not occur in animals that received oral acetaminophen at doses 0.3-times the MHDD, based on a body surface area comparison.

In a continuous breeding study, pregnant mice received 0.25, 0.5, or 1.0% acetaminophen via the diet (357, 715, or 1430 mg/kg/day). These doses are approximately 0.45, 0.89, and 1.8 times the MHDD, respectively, based on a body surface area comparison. A dose-related reduction in body weights of fourth and fifth litter offspring of the treated mating pair occurred during lactation and post-weaning at all doses. Animals in the high dose group had a reduced number of litters per mating pair, male offspring with an increased percentage of abnormal sperm, and reduced birth weights in the next generation pups.

8.2 Lactation

Risk Summary

The components of COMBOGESIC, ibuprofen and acetaminophen, are present in human milk. Limited published literature reports that, orally administered ibuprofen is present in human milk at relative infant doses of 0.06% to 0.6% of the maternal weight-adjusted daily dose. There are no reports of adverse effects of ibuprofen on the breastfed infant and no effects on milk production.

Limited published studies report that orally administered acetaminophen passes rapidly into human milk with similar levels in the milk and plasma. Average and maximum neonatal doses of 1% and 2%, respectively, of the weight-adjusted maternal dose are reported after a single oral administration of 1 gram acetaminophen. There is one well-documented report of a rash in a breast-fed infant that resolved when the mother stopped acetaminophen use and recurred when she resumed acetaminophen use.

The developmental and health benefits of breastfeeding should be considered along with the mother's clinical need for COMBOGESIC and any potential adverse effects on the breastfed infant from COMBOGESIC or from the underlying maternal condition.

8.3 Females and Males of Reproductive Potential

Infertility

Ibuprofen

Based on the mechanism of action, the use of prostaglandin mediated NSAID-containing products, including COMBOGESIC, may delay or prevent rupture of ovarian follicles, which has been associated with reversible infertility in some women. Published animal studies have shown that administration of prostaglandin synthesis inhibitors has the potential to disrupt prostaglandin mediated follicular rupture required for ovulation. Small studies in women treated with NSAIDs have also shown a reversible delay in ovulation. Consider withdrawal of NSAID containing products, including COMBOGESIC in women who have difficulties conceiving or who are undergoing investigation of infertility.

Acetaminophen

Based on animal data, use of acetaminophen may cause reduced fertility in males and females of reproductive potential. It is not known whether these effects on fertility are reversible.

Published studies in rodents report that oral acetaminophen treatment of male animals at doses that are approximately 1.2 times the MHDD and greater (based on a body surface area comparison) result in decreased testicular weights, reduced spermatogenesis, and reduced fertility. In female animals given the same doses, reduced implantation sites were reported. Additional published animal studies indicate that acetaminophen exposure in utero adversely impacts reproductive capacity of both male and female offspring at clinically relevant exposures [see Nonclinical Toxicology (13.1)].

8.4 Pediatric Use

The safety and effectiveness of COMBOGESIC in pediatric patients have not been established. COMBOGESIC is not approved for patients under 18 years of age.

8.5 Geriatric Use

Elderly patients, compared to younger patients, are at greater risk for NSAID-associated serious cardiovascular, gastrointestinal, and/or renal adverse reactions. If the anticipated benefit for the elderly patient outweighs these potential risks, start dosing at the low end of the dosing range, and monitor patients for adverse effects [see Warnings and Precautions (5.1, 5.2, 5.3, 5.4, 5.5, 5.6)].

This drug is known to be substantially excreted by the kidney, and the risk of adverse reactions to this drug may be greater in patients with impaired renal function. Because elderly patients are more likely to have decreased renal function, care should be taken in dose selection, and it may be useful to monitor renal function.

8.6 Use in Renal Disease

COMBOGESIC has not been studied in patients with impaired renal function. The use of COMBOGESIC in patients with renal impairment is not recommended [see Warnings and Precautions (5.6)].

8.7 Use in Hepatic Disease

COMBOGESIC has not been studied in patients with impaired hepatic function. The use of COMBOGESIC in patients with hepatic impairment is not recommended [see Warnings and Precautions (5.1)].

10 OVERDOSAGE

COMBOGESIC is a combination product. The clinical presentation of overdose may include the signs and symptoms of acetaminophen toxicity, ibuprofen toxicity, or both.

Acetaminophen

The initial symptoms seen within the first 24 hours following an acetaminophen overdose are: anorexia, nausea, vomiting, malaise, pallor and diaphoresis. Clinical and laboratory evidence of hepatic toxicity may not be apparent until 48 to 72 hours post-ingestion.

In acute acetaminophen overdosage, dose-dependent, potentially fatal hepatic necrosis is the most serious adverse effect. Renal tubular necrosis, hypoglycemic coma, and coagulation defects also may occur. Plasma acetaminophen levels >300 mcg/mL at 4 hours after oral ingestion were associated with hepatic damage in 90% of patients; minimal hepatic damage is anticipated if plasma levels at 4 hours are <150 mcg/mL or <37.5 mcg/mL at 12 hours after ingestion.

If an acetaminophen overdose is suspected, obtain a serum acetaminophen assay as soon as possible, but no sooner than 4 hours following oral ingestion. Obtain liver function studies initially and repeat at 24-hour intervals. Administer the antidote N-acetylcysteine (NAC) as early as possible. As a guide to treatment of acute ingestion, the acetaminophen level can be plotted against time since oral ingestion on a nomogram Rumack-Matthew). The lower toxic line on the nomogram is equivalent to 150 mcg/mL at 4 hours and 37.5 mcg/mL at 12 hours. If serum level is above the lower line, administer the entire course of NAC treatment. Withhold NAC therapy if the acetaminophen level is below the lower line.

Ibuprofen

Symptoms following acute NSAID overdosages have been typically limited to lethargy, drowsiness, nausea, vomiting, and epigastric pain, which have been generally reversible with supportive care. Gastrointestinal bleeding has occurred. Hypertension, acute renal failure, respiratory depression, and coma have occurred, but were rare [see Warnings and Precautions (5.1, 5.2, 5.3, 5.4, 5.6, 5.14)].

Manage patients with symptomatic and supportive care following an NSAID overdosage. There are no specific antidotes. It is advisable to contact a poison control center (1-800-222-1222) to determine the latest recommendations because strategies for the management of overdose are continually evolving.

If gastric decontamination may benefit the patient, e.g., short time since ingestion or a large overdosage (5 to 10 times the recommended dosage), consider emesis and/or activated charcoal (60 to 100 grams in adults, 1 to 2 grams per kg of body weight in pediatric patients) and/or an osmotic cathartic in symptomatic patients if clinically appropriate.

11 DESCRIPTION

COMBOGESIC tablets are a combination of acetaminophen, an analgesic and antipyretic, and ibuprofen, a non-steroidal anti-inflammatory drug (NSAID).

The chemical name for acetaminophen is N-acetyl-p-aminophenol. The molecular formula is C8H9NO2 and the structural formula is:

The molecular weight of acetaminophen is 151.17. Acetaminophen is a white, odorless, crystalline powder, possessing a slightly bitter taste. Acetaminophen is soluble in boiling water and 1N sodium hydroxide, and is freely soluble in alcohol.

The chemical name for ibuprofen is (±)-2-(p-isobutylphenyl) propionic acid. The molecular formula is C13H18O2 and the structural formula is:

The molecular weight of ibuprofen is 206.29. Ibuprofen is a white powder with a melting point of 74-77°C and is very slightly soluble in water (<1 mg/mL) and readily soluble in organic solvents such as ethanol and acetone.

COMBOGESIC tablets contain 325 mg acetaminophen and 97.5 mg ibuprofen and are white in color. The inactive ingredients in the tablet are croscarmellose sodium, hypromellose, lactose monohydrate, magnesium stearate, maltodextrin, medium chain triglycerides, microcrystalline cellulose, polydextrose, povidone-30, sodium lauryl sulfate, talc, titanium dioxide.

12 CLINICAL PHARMACOLOGY

12.1 Mechanism of Action

Analgesia

COMBOGESIC contains acetaminophen and ibuprofen.

Acetaminophen is a non-opiate, non-salicylate analgesic. The precise mechanism of the analgesic properties of acetaminophen is not established but is thought to primarily involve central actions. Ibuprofen is a nonsteroidal anti-inflammatory drug (NSAID). Its mechanism of action for analgesia, like that of other NSAIDs, is not completely understood, but involves inhibition of cyclooxygenase (COX-1 and COX-2).

Ibuprofen is a potent inhibitor of prostaglandin synthesis in vitro. Prostaglandins sensitize afferent nerves and potentiate the action of bradykinin in inducing pain in animal models. Prostaglandins are mediators of inflammation. Because ibuprofen is an inhibitor of prostaglandin synthesis, its mode of action may be due to a decrease of prostaglandins in peripheral tissues.

12.2 Pharmacodynamics

Hematological Effects

NSAIDs inhibit platelet aggregation and have been shown to prolong bleeding time in some patients. Unlike aspirin, their effect on platelet function is quantitatively less, of shorter duration, and reversible.

12.3 Pharmacokinetics

Absorption

Peak plasma concentration following the administration of three COMBOGESIC tablets occurs at approximately 45 minutes and 1 hour 15 minutes after administration for acetaminophen and ibuprofen, respectively, under fasting condition. In the same study, the peak plasma concentration (Cmax) and the extent of absorption (AUC0-inf) are 14.88 mcg/mL and 47.44 mcg.h/mL for acetaminophen and 25.58 mcg/mL and 95.62 mcg.h/mL for ibuprofen, respectively. The Cmax and AUC0-inf values for both acetaminophen and ibuprofen increase dose proportionally to increases in COMBOGESIC doses from one, to two, to three tablets. A single-dose pharmacokinetic study of COMBOGESIC in volunteers showed no drug interactions between acetaminophen and ibuprofen.

Food effects

When COMBOGESIC was administered with food, the time to peak plasma concentration was delayed by approximately 30 minutes for acetaminophen and was approximately the same when compared to fasting conditions for ibuprofen. The peak plasma concentration of acetaminophen was reduced by approximately 30%, but the extent of absorption was not affected. Peak plasma concentration and the extent of absorption were not affected for ibuprofen.

Distribution

Acetaminophen appears to be widely distributed throughout most body tissues except fat. Its apparent volume of distribution is about 0.9 L/kg. A relatively small portion (~20%) of acetaminophen is bound to plasma protein.

Elimination

The half-life of acetaminophen is about 2 to 3 hours in adults. It is somewhat shorter in children and somewhat longer in neonates and in cirrhotic patients. Acetaminophen is eliminated from the body primarily by formation of glucuronide and sulfate conjugates in a dose-dependent manner.

Ibuprofen is rapidly metabolized and eliminated in the urine. The elimination half-life of ibuprofen is in the range of 1.9 to 2.2 hours.

Metabolism

Acetaminophen is primarily metabolized in the liver by first-order kinetics and involves three principal separate pathways:

1. conjugation with glucuronide;
2. conjugation with sulfate; and
3. oxidation via the cytochrome, P450-dependent, mixed-function oxidase enzyme pathway to form a reactive intermediate metabolite, which conjugates with glutathione and is then further metabolized to form cysteine and mercapturic acid conjugates. The principal cytochrome P450 isoenzyme involved appears to be CYP2E1, with CYP1A2 and CYP3A4 as additional pathways.

In adults, the majority of acetaminophen is conjugated with glucuronic acid and, to a lesser extent, with sulfate. These glucuronide-, sulfate-, and glutathione-derived metabolites lack biologic activity. In premature infants, newborns, and young infants, the sulfate conjugate predominates.

Excretion

Less than 9% of acetaminophen is excreted unchanged in the urine.

The excretion of ibuprofen is virtually complete 24 hours after the last dose. Studies have shown that following ingestion of ibuprofen 45% to 79% of the dose was recovered in the urine within 24 hours as metabolite A (25%), (+)-2-[p-(2hydroxymethyl-propyl) phenyl]propionic acid and metabolite B (37%), (+)-2-[p-(2carboxypropyl)phenyl]propionic acid; the percentages of free and conjugated ibuprofen were approximately 1% and 14%, respectively.

Specific Populations

Pediatric Patients

The pharmacokinetics of COMBOGESIC has not been studied in pediatric patients below 18 years of age.

Hepatic Impairment

The pharmacokinetics of COMBOGESIC in patients with impaired hepatic function has not been studied [see Warnings and Precautions (5.1) and Use in Specific Populations (8.7)].

Renal Impairment

The pharmacokinetics of COMBOGESIC in patients with renal impairment has not been studied. [see Warnings and Precautions (5.6) and Use in Specific Populations (8.6)].

Drug Interaction Studies

Aspirin: When ibuprofen is administered with aspirin, its protein binding is reduced, although the clearance of free ibuprofen is not altered. The clinical significance of this interaction is not known [see Drug Interactions (7)].

13 NONCLINICAL TOXICOLOGY

13.1 Carcinogenesis, Mutagenesis, and Impairment of Fertility

Studies to evaluate the potential effects of COMBOGESIC on carcinogenicity, mutagenicity, or impairment of fertility have not been conducted.

Carcinogenesis

Acetaminophen

Long-term studies in mice and rats have been completed by the National Toxicology Program to evaluate the carcinogenic potential of acetaminophen. In 2-year feeding studies, F344/N rats and B6C3F1 mice were fed a diet containing acetaminophen up to 6000 ppm. Female rats demonstrated equivocal evidence of carcinogenic activity based on increased incidences of mononuclear cell leukemia at 0.8 times the maximum human daily dose (MHDD) of 3.9 grams/day, based on a body surface area comparison. In contrast, there was no evidence of carcinogenic activity in male rats (0.7 times) or mice (1.3-1.5 times the MHDD, based on a body surface area comparison).

Ibuprofen

Adequate long-term animal studies have not been conducted to evaluate the carcinogenic potential of ibuprofen.

Mutagenesis

Acetaminophen

Acetaminophen was not mutagenic in the bacterial reverse mutation assay (Ames test). In contrast, acetaminophen tested positive in the in vitro mouse lymphoma assay and the in vitro chromosomal aberration assay using human lymphocytes. In the published literature, acetaminophen has been reported to be clastogenic when administered a dose of 1500 mg/kg/day to the rat model (3.7-times the MHDD, based on a body surface area comparison). In contrast, no clastogenicity was noted at a dose of 750 mg/kg/day (1.9-times the MHDD, based on a body surface area comparison), suggesting a threshold effect.

Ibuprofen

In published studies, ibuprofen was not mutagenic in the in vitro bacterial reverse mutation assay (Ames assay).

Impairment of Fertility

Acetaminophen

In studies of acetaminophen conducted by the National Toxicology Program, fertility assessments with acetaminophen have been completed in Swiss mice via a continuous breeding study. There were no effects on fertility parameters in mice consuming up to 1.8 times the MHDD of acetaminophen, based on a body surface area comparison. Although there was no effect on sperm motility or sperm density in the epididymis, there was a significant increase in the percentage of abnormal sperm in mice consuming 1.8 times the MHDD (based on a body surface area comparison) and there was a reduction in the number of mating pairs producing a fifth litter at this dose, suggesting the potential for cumulative toxicity with chronic administration of acetaminophen near the upper limit of daily dosing.

Published studies in rodents report that oral acetaminophen treatment of male animals at doses that are 1.2 times the MHDD and greater (based on a body surface area comparison) result in decreased testicular weights, reduced spermatogenesis, reduced fertility, and reduced implantation sites in females given the same doses. These effects appear to increase with the duration of treatment.

In a published mouse study, oral administration of 50 mg/kg acetaminophen to pregnant mice from Gestation Day 7 to delivery (0.062 times the MHDD) reduced the number of primordial follicles in female offspring and reduced the percentage of full term pregnancies and number of pups born to these females exposed to acetaminophen in utero.

In a published study, pregnant rats oral administration of 350 mg/kg acetaminophen (0.87 times the MHDD) from Gestation Day 13 to 21 (dams), reduced the number of germ cells in the fetal ovary and decreased ovary weight and reduced number of pups per litter in F1 females as well as reduced ovary weights in F2 females.

Ibuprofen

In a published study, dietary administration of ibuprofen to male and female rats 8-weeks prior to and during mating at dose levels of 20 mg/kg (0.17-times the MHDD based on body surface area comparison) did not impact male or female fertility or litter size.

In other studies, adult mice were administered ibuprofen intraperitoneally at a dose of 5.6 mg/kg/day (0.023-times the MHDD based on a body surface area comparison) for 35 or 60 days in males and 35 days in females. There was no effect on sperm motility or viability in males, but decreased ovulation was reported in females.

14 CLINICAL STUDIES

In a Phase 3 efficacy study in 110 patients (aged from 16 to 55 years, approximately two-thirds female, and more than 80% Caucasian) with post-procedural pain following surgical extraction of impacted wisdom teeth, three tablets of COMBOGESIC provided greater pain reduction than placebo or comparable doses of acetaminophen or ibuprofen alone. The treatment differences were measured by the primary end point.

The treatment differences in the time-adjusted Summed Pain Intensity Difference over the first 48 hours (SPID 0-48), are statistically significant as summarized in the table below.

Table 3: Summary of Time-adjusted SPID (0-48 Hours) by Treatment Group
 | Ibuprofen 97.5 mg | Acetaminophen 325 mg | Placebo | COMBOGESIC
 | N=112 | N=111 | N=75 | N=110
Mean | 23.18 | 17.71 | 14.86 | 31.56
SE | 1.89 | 1.89 | 2.26 | 1.94
95% CI (Lower) | 19.47 | 14.00 | 10.43 | 27.76
95% (Upper) | 26.89 | 21.43 | 19.30 | 35.37
P-value COMBOGESIC | <0.001 | <0.001 | <0.001 | -

The observed treatment differences over the first six hours are illustrated by the separation of pain curves as shown in Figure 1 below.

Figure 1: Pain Intensity Differences from baseline over the first dose interval of AFT-MX-6

16 HOW SUPPLIED/STORAGE AND HANDLING

COMBOGESIC tablets with acetaminophen 325 mg and ibuprofen 97.5 mg are white, biconvex, capsule-shaped film coated tablets, debossed with the letters "CG" on one side and plain on the other side and are available as follows:

NDC 68788-4009-1 | 1 bottle containing 120 tablets

STORAGE AND HANDLING

Store at 20°C to 25°C (68°F to 77°F) with excursions permitted within USP controlled room temperature of 15°C to 30°C (59°F to 86°F). Protect from moisture and light.

17 PATIENT COUNSELING INFORMATION

Advise the patient to read the FDA-approved patient labeling (Medication Guide).

Important Dosage and Administration Information:

- Clearly explain to patients the single-dose and 24-hour dose limit and the time interval between doses. Explain that exceeding these recommendations can result in hepatic toxicity and/or gastrointestinal bleeding, ulceration, and perforation [See Dosage and Administration (2), Warnings and Precautions (5.1, 5.3)].
- Inform patients that the concomitant use of COMBOGESIC with other NSAIDs, acetaminophen-containing products, or salicylates (e.g., diflunisal, salsalate) is not recommended due to the increased risk of hepatic and gastrointestinal toxicity, and little or no increase in efficacy [see Warnings and Precautions (5.1, 5.3), Drug Interactions (7)]. Alert patients that these may be present in "over the counter" medications for treatment of colds, fever, or insomnia.
- Alert patients that NSAIDs and acetaminophen may be present in "over the counter" medications for treatment of colds, fever, or insomnia.

Hepatotoxicity: Inform patients of the warning signs and symptoms of hepatotoxicity (e.g., nausea, fatigue, lethargy, pruritus, jaundice, right upper quadrant tenderness and "flu-like" symptoms). Instruct patients to stop therapy and seek immediate medical assistance if these occur [see Warnings and Precautions (5.1)].

Alcohol: Advise patients not to take COMBOGESIC concomitantly with alcohol-containing beverages [see Warnings and Precautions (5.1)].

Cardiovascular Thrombotic Effects: Inform patients that COMBOGESIC, like other NSAID-containing medications, may cause serious CV side effects such as MI or stroke, which may result in hospitalization and even death. Advise patients to be alert for chest pain, shortness of breath, weakness, and slurring of speech, and to seek medical assistance when observing any sign or symptom indicative of CV effects [see Warnings and Precautions (5.2)].

Gastrointestinal Bleeding, Ulceration, and Perforation: Inform patients that COMBOGESIC, like other NSAID-containing medications, can cause GI discomfort and, rarely, serious GI side effects, such as ulcers and bleeding, which may result in hospitalization and even death. Advise patients to be alert for the signs and symptoms of ulcerations and bleeding, including epigastric pain, dyspepsia, melena, and hematemesis, and to seek medical assistance should these symptoms occur [see Warnings and Precautions (5.3)].

Heart Failure and Edema: Advise patients to be alert for the symptoms of congestive heart failure including shortness of breath, unexplained weight gain, or edema and to contact their healthcare provider if such symptoms occur [see Warnings and Precautions (5.5)].

Weight Gain and Edema: Advise patients to promptly report unexplained weight gain or edema to their physicians [see Warnings and Precautions (5.5)].

Anaphylactic Reactions: Inform patients of the signs of an anaphylactic reaction (e.g., difficulty breathing, swelling of the face or throat). Instruct patients to seek immediate emergency help if these occur [see Warnings and Precautions (5.7)].

Serious Skin Reactions, including DRESS: Advise patients to stop taking COMBOGESIC immediately if they develop any type of rash or fever and to contact their healthcare provider as soon as possible [see Warnings and Precautions (5.9, 5.10)].

Female Fertility: Advise females of reproductive potential who desire pregnancy that NSAID containing products, including COMBOGESIC tablets, may be associated with a reversible delay in ovulation [see Use in Specific Populations (8.3)].

Fetal Toxicity: Inform pregnant women to avoid use of COMBOGESIC and other NSAIDs starting at 30 weeks gestation because of the risk of the premature closing of the fetal ductus arteriosus. If treatment with COMBOGESIC is needed for a pregnant woman between about 20 to 30 weeks gestation, advise her that she may need to be monitored for oligohydramnios, if treatment continues for longer than 48 hours [see Warnings and Precautions (5.11) and Use in Specific Populations (8.1)].

Use of NSAIDS and Low-Dose Aspirin: Inform patients not to use low-dose aspirin concomitantly with COMBOGESIC until they talk to their healthcare provider [see Drug Interactions (7)].

Manufactured by: Catalent Greenville Inc., 1240 Sugg Parkway, Greenville, NC 27834

Distributed by: AFT Pharmaceuticals US, Inc., 42714 Woodward Ave, Suite B, Bloomfield Hills, MI 48304.

Repackaged By: Preferred Pharmaceuticals Inc.

Medication Guide
COMBOGESIC (kom-boh-JEE-zik)
(acetaminophen and ibuprofen)
tablets

COMBOGESIC is a combination prescription medicine that contains acetaminophen and ibuprofen (a nonsteroidal anti-inflammatory drug [NSAID]).

What is the most important information I should know about COMBOGESIC?
COMBOGESIC may cause serious side effects, including:

- Severe liver problems. Acetaminophen, one of the ingredients in COMBOGESIC, has caused severe and life-threatening acute liver failure which caused the need for a liver transplant and has caused death.
  - Taking COMBOGESIC with other products that contain acetaminophen can lead to serious severe liver problems and death. Do not take COMBOGESIC with other acetaminophen containing products.
  - You should not take more than 3 COMBOGESIC tablets in one dose or more than 12 COMBOGESIC tablets in one day.
  - If you take too much COMBOGESIC or acetaminophen, call your healthcare provider or Poison Control Center at 1-800-222-1222, or go to the nearest hospital emergency room right away.
- Increased risk of a heart attack or stroke that can lead to death. This risk may happen early in treatment and may increase:Do not take COMBOGESIC right before or after a heart surgery called a "coronary artery bypass graft (CABG)."
  Avoid taking COMBOGESIC after a recent heart attack unless your healthcare provider tells you to. You may have an increased risk of another heart attack if you take COMBOGESIC after a recent heart attack.
  - with increasing doses of medicines containing NSAIDs
  - with longer use of medicines containing NSAIDs
- Increased risk of bleeding, ulcers, and tears (perforation) of the esophagus (tube leading from the mouth to the stomach), stomach and intestines:The risk of getting an ulcer or bleeding increases with:COMBOGESIC should only be taken exactly as prescribed, at the lowest dose possible for your treatment, and for the shortest time needed.
  - anytime during use
  - without warning symptoms
  - that may cause death
  - past history of stomach ulcers, or stomach or intestinal bleeding with use of NSAIDs
  - taking medicines called "corticosteroids", "anticoagulants", "SSRIs", or "SNRIs"
  - increasing doses of NSAIDs
  - longer use of NSAIDs
  - smoking
  - drinking alcohol
  - older age
  - poor health
  - advanced liver disease
  - bleeding problems

What is COMBOGESIC?
COMBOGESIC is a combination prescription medicine that contains acetaminophen and ibuprofen (a non-steroidal anti-inflammatory drug [NSAID]) used in adults for the short-term management of mild to moderate acute pain.
It is not known if COMBOGESIC is safe and effective for use in children.

Do not take COMBOGESIC:

- If you are allergic to acetaminophen, ibuprofen, other NSAIDs, or to any of the ingredients in COMBOGESIC. See the end of this Medication Guide for a complete list of ingredients in COMBOGESIC.
- If you have had an asthma attack, hives, or other allergic reactions after taking aspirin or any other NSAIDs.
- Right before or after heart bypass surgery.

Before taking COMBOGESIC, tell your healthcare provider about all of your medical conditions, including if you:

- have liver or kidney problems
- have high blood pressure
- have asthma
- have heart problems
- have bleeding problems
- have or have had ulcers
- drink alcohol
- are pregnant or plan to become pregnant. Taking COMBOGESIC at about 20 weeks of pregnancy or later may harm your unborn baby.
  - If you need to take NSAIDs for more than 2 days when you are between 20 and 30 weeks of pregnancy, your healthcare provider may need to monitor the amount of fluid in your womb around your baby. You should not take NSAIDs after about 30 weeks of pregnancy.
  - NSAID containing products, including COMBOGESIC, may cause reversible fertility problems in females, which may temporarily affect your ability to become pregnant during treatment with COMBOGESIC. Talk to your healthcare provider if this is a concern for you.
- are breastfeeding or plan to breastfeed. Ibuprofen can pass into your breast milk. Talk to your healthcare provider about the best way to feed your baby during treatment with COMBOGESIC.

Tell your healthcare provider about all of the medicines you take, including prescription and over-the-counter medicines, vitamins, and herbal supplements.
COMBOGESIC and some other medicines can interact with each other and cause serious side effects. Do not start taking any new medicine without talking to your healthcare provider first.

How should I take COMBOGESIC?

- Take COMBOGESIC exactly as your healthcare provider tells you to take it.
- You should not take more than 3 COMBOGESIC tablets in one dose or more than 12 COMBOGESIC tablets each day.
- If you take too much COMBOGESIC, call your healthcare provider or Poison Control Center at 1-800-222-1222, or go to the nearest hospital emergency room right away.

What should I avoid while taking COMBOGESIC?

- You should avoid drinking alcohol during treatment with COMBOGESIC. Drinking alcohol during treatment with COMBOGESIC may increase your chances of having serious side effects.

What are the possible side effects of COMBOGESIC?
COMBOGESIC may cause serious side effects, including:
See "What is the most important information I should know about COMBOGESIC?"

- new or worse high blood pressure
- heart failure
- liver problems including liver failure
- kidney problems including kidney failure
- high potassium level in your blood (hyperkalemia)
- life-threatening allergic reactions
- life-threatening skin reactions
- low red blood cells (anemia)
- changes in your vision

Other side effects of COMBOGESIC include: nausea, vomiting, headache, dizziness, sleepiness, bleeding after medical procedures, swelling of the face.
Get emergency help right away if you get any of the following symptoms:

- shortness of breath or trouble breathing
- slurred speech
- chest pain
- swelling of the face or throat
- weakness in one part or side of your body

Stop taking COMBOGESIC and call your healthcare provider right away if you get any of the following symptoms:

- nausea
- vomit blood
- more tired or weaker than usual
- there is blood in your bowel movement or it is black and sticky like tar
- diarrhea
- itching
- unusual weight gain
- your skin or eyes look yellow
- skin rash or blisters with fever (including rash with hives, sores in your mouth or eyes, or your skin blisters and peels)
- indigestion or stomach pain
- swelling of the arms, legs, hands, and feet
- flu-like symptoms
These are not all the possible side effects of COMBOGESIC.
  Call your doctor for medical advice about side effects. You may report side effects to FDA at 1-800-FDA-1088.

Other information about NSAIDs

- Aspirin is an NSAID but it does not increase the chance of a heart attack. Aspirin can cause bleeding in the brain, stomach, and intestines. Aspirin can also cause ulcers in the stomach and intestines.
- Some NSAIDs are sold in lower doses without a prescription (over-the-counter). Talk to your healthcare provider before using over-the-counter NSAIDs for more than 10 days.

General information about the safe and effective use of COMBOGESIC.
Medicines are sometimes prescribed for purposes other than those listed in a Medication Guide. Do not use COMBOGESIC for a condition for which it was not prescribed. Do not give COMBOGESIC to other people, even if they have the same symptoms that you have. It may harm them. You can ask your pharmacist or healthcare provider for information about COMBOGESIC that is written for health professionals.

What are the ingredients in COMBOGESIC?
Active ingredients: acetaminophen and ibuprofen
Inactive ingredients: croscarmellose sodium, hypromellose, lactose monohydrate, magnesium stearate, maltodextrin, medium chain triglycerides, microcrystalline cellulose, polydextrose, povidone-30, sodium lauryl sulfate, talc, titanium dioxide.

Manufactured by: Catalent Greenville Inc, 1240 Sugg Parkway, Greenville, NC 27834. Ph: +1-252-752-3800
Distributed by: AFT Pharmaceuticals US, Inc. 42714 Woodward Ave, Suite B, Bloomfield Hills, MI 48304. Ph: 01-248-631-4810
For more information go to www.aftpharm.com or call: 01-248-631-4810

This Medication Guide has been approved by the U.S. Food and Drug Administration.

Issued: 11/2024

Repackaged By: Preferred Pharmaceuticals Inc.

PRINCIPAL DISPLAY PANEL - 325 mg/97.5 mg Tablet Bottle Label

NDC 68788-4009-1
Rx only

combogesic®

(acetaminophen and ibuprofen)
Tablets 325 mg/97.5 mg

120 Film-coated tablets

ATTENTION PHARMACIST: EACH PATIENT IS
REQUIRED TO RECEIVE THE MEDICATION
GUIDE PROVIDED SEPARATELY

AFT pharmaceutical Repackaged By: Preferred Pharmaceuticals Inc.